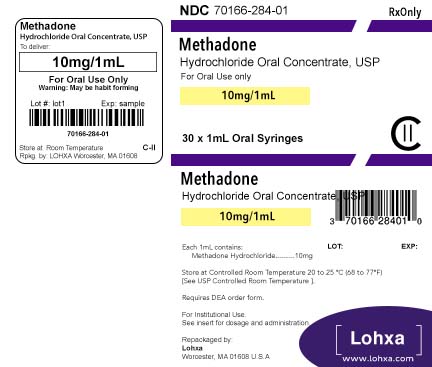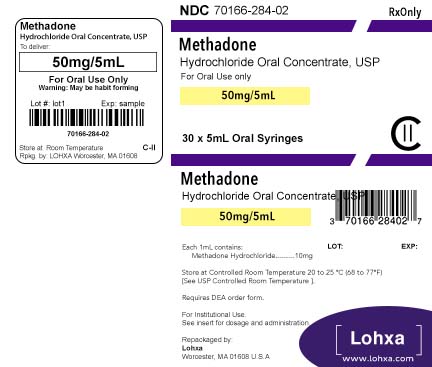 DRUG LABEL: Methadone Hydrochloride
NDC: 70166-284 | Form: CONCENTRATE
Manufacturer: Lohxa
Category: prescription | Type: HUMAN PRESCRIPTION DRUG LABEL
Date: 20190910
DEA Schedule: CII

ACTIVE INGREDIENTS: METHADONE HYDROCHLORIDE 10 mg/1 mL
INACTIVE INGREDIENTS: CITRIC ACID MONOHYDRATE; WATER; SODIUM BENZOATE

Methadone Hydrochloride Oral Concentrate USP CII, 10 mg per mL
(Dye-Free, Sugar-Free, Unflavored)

FOR ORAL USE ONLY

Rx only

Regulatory Exceptions to the General Requirement for Certification to Provide Opioid Agonist Treatment:

1. During inpatient care, when the patient was admitted for any condition other than concurrent opioid addiction (pursuant to 21 CFR 1306.07(c)), to facilitate the treatment of the primary admitting diagnosis.
2. During an emergency period of no longer than 3 days while definitive care for the addiction is being sought in an appropriately licensed facility (pursuant to 21 CFR 1306.07(b)).

Click here to enter boxed warning title

Deaths have been reported during initiation of methadone treatment for opioid dependence. In some cases, drug interactions with other drugs, both licit and illicit, have been suspected. However, in other cases, deaths appear to have occurred due to the respiratory or cardiac effects of methadone and too-rapid titration without appreciation for the accumulation of methadone over time. It is critical to understand the pharmacokinetics of methadone and to exercise vigilance during treatment initiation and dose titration (see DOSAGE AND ADMINISTRATION). Patients must also be strongly cautioned against self-medicating with CNS depressants during initiation of methadone treatment.

Respiratory depression is the chief hazard associated with methadone hydrochloride administration. Methadone's peak respiratory depressant effects typically occur later, and persist longer than its peak analgesic effects, particularly in the early dosing period. These characteristics can contribute to cases of iatrogenic overdose, particularly during treatment initiation and dose titration.

Cases of QT interval prolongation and serious arrhythmia (torsades de pointes) have been observed during treatment with methadone. Most cases involve patients being treated for pain with large, multiple daily doses of methadone, although cases have been reported in patients receiving doses commonly used for maintenance treatment of opioid addiction.

Conditions for Distribution and Use of Methadone Products for the Treatment of Opioid Addiction Code of Federal Regulations, Title 42, Sec 8

METHADONE PRODUCTS WHEN USED FOR THE TREATMENT OF OPIOID ADDICTION IN DETOXIFICATION OR MAINTENANCE PROGRAMS, SHALL BE DISPENSED ONLY BY OPIOID TREATMENT PROGRAMS (AND AGENCIES, PRACTITIONERS OR INSTITUTIONS BY FORMAL AGREEMENT WITH THE PROGRAM SPONSOR) CERTIFIED BY THE SUBSTANCE ABUSE AND MENTAL HEALTH SERVICES ADMINISTRATION AND APPROVED BY THE DESIGNATED STATE AUTHORITY. CERTIFIED TREATMENT PROGRAMS SHALL DISPENSE AND USE METHADONE IN ORAL FORM ONLY AND ACCORDING TO THE TREATMENT REQUIREMENTS STIPULATED IN THE FEDERAL OPIOID TREATMENT STANDARDS (42 CFR 8.12). See below for important regulatory exceptions to the general requirement for certification to provide opioid agonist treatment.

FAILURE TO ABIDE BY THE REQUIREMENTS IN THESE REGULATIONS MAY RESULT IN CRIMINAL PROSECUTION, SEIZURE OF THE DRUG SUPPLY, REVOCATION OF THE PROGRAM APPROVAL, AND INJUNCTION PRECLUDING OPERATION OF THE PROGRAM.

DESCRIPTION

Each mL for oral administration contains 10 mg methadone hydrochloride USP. Methadone hydrochloride is chemically described as 6-(dimethylamino)-4,4-diphenyl-3-hepatanone hydrochloride. Methadone hydrochloride USP is a white, crystalline material that is water-soluble. Its molecular formula is C21H27NO•HCl and it has a molecular weight of 345.91. Methadone hydrochloride has a melting point of 235°C, and a pKa of 8.25 in water at 20°C. Its octanol/water partition coefficient at pH 7.4 is 117. A solution (1:100) in water has a pH between 4.5 and 6.5.

It has the following structural formula:

Each mL of the unflavored liquid concentrate, for oral administration, contains 10 mg of methadone hydrochloride USP. The Inactive ingredients are: citric acid, sodium benzoate and water.

Each mL of the cherry flavored liquid concentrate, for oral administration, contains 10 mg of methadone hydrochloride USP. The inactive ingredients are: citric acid, cherry pistachio flavor, D&C Red #33, FD&C Red #40, glycerin, propylene glycol, saccharin sodium, sodium benzoate, sorbitol solution, sucrose and water.

Mechanism of Action

Methadone hydrochloride is a mu-agonist; a synthetic opioid analgesic with multiple actions qualitatively similar to those of morphine, the most prominent of which involves the central nervous system and organs composed of smooth muscle. The principal therapeutic uses for methadone are analgesia and detoxification or maintenance treatment in opioid addiction. The methadone abstinence syndrome, although qualitatively similar to that of morphine, differs in that the onset is slower, the course is more prolonged, and the symptoms are less severe.

Some data also indicate that methadone acts as an antagonist at the N-methyl-D-aspartate (NMDA) receptor. The contribution of NMDA receptor antagonism to methadone’s efficacy is unknown. Other NMDA receptor antagonists have been shown to produce neurotoxic effects in animals.

Pharmacokinetics

Absorption

Following oral administration the bioavailability of methadone ranges between 36 to 100% and peak plasma concentrations are achieved between 1 to 7.5 hours. Dose proportionality of methadone pharmacokinetics is not known. However, after administration of daily oral doses ranging from 10 to 225 mg, the steady-state plasma concentrations ranged between 65 to 630 ng/mL and the peak concentrations ranged between 124 to 1255 ng/mL. Effect of food on the bioavailability of methadone has not been evaluated.

Distribution

Methadone is a lipophilic drug and the steady-state volume of distribution ranges between 1.0 to 8.0 L/kg. In plasma, methadone is predominantly bound to α1-acid glycoprotein (85% to 90%). Methadone is secreted in saliva, breast milk, amniotic fluid and umbilical cord plasma.

Metabolism

Methadone is primarily metabolized by N-demethylation to an inactive metabolite, 2-ethylidene-1,5-dimethyl-3,3-diphenylpyrrolidene (EDDP). Cytochrome P450 enzymes, primarily CYP3A4, CYP2B6, CYP2C19, and to a lesser extent CYP2C9 and CYP2D6, are responsible for conversion of methadone to EDDP and other inactive metabolites, which are excreted mainly in the urine.

Excretion

The elimination of methadone is mediated by extensive biotransformation, followed by renal and fecal excretion. Published reports indicate that after multiple dose administration the apparent plasma clearance of methadone ranged between 1.4 to 126 L/h, and the terminal half-life (T1/2) was highly variable and ranged between 8 and 59 hours in different studies. Since methadone is lipophilic, it has been known to persist in the liver and other tissues. The slow release from the liver and other tissues may prolong the duration of methadone action despite low plasma concentrations.

Pharmacokinetics in Special Populations

Pregnancy

The disposition of oral methadone has been studied in approximately 30 pregnant patients in the second and third trimesters. Elimination of methadone was significantly changed in pregnancy. Total body clearance of methadone was increased in pregnant patients compared to the same patients postpartum or to non-pregnant opioid-dependent women. The terminal half-life of methadone is decreased during second and third trimesters. The decrease in plasma half-life and increased clearance of methadone resulting in lower methadone trough levels during pregnancy can lead to withdrawal symptoms in some pregnant patients. The dosage may need to be increased or the dosing interval decreased in pregnant patients receiving methadone. (See PRECAUTIONS : Pregnancy, Labor and Delivery , and DOSAGE AND ADMINISTRATION.)

Renal Impairment

Methadone pharmacokinetics have not been extensively evaluated in patients with renal insufficiency. Unmetabolized methadone and its metabolites are excreted in urine to a variable degree. Methadone is a basic (pKa=9.2) compound and the pH of the urinary tract can alter its disposition in plasma. Urine acidification has been shown to increase renal elimination of methadone. Forced diuresis, peritoneal dialysis, hemodialysis, or charcoal hemoperfusion have not been established as beneficial for increasing the elimination of methadone or its metabolites.

Hepatic Impairment

Methadone has not been extensively evaluated in patients with hepatic insufficiency. Methadone is metabolized by hepatic pathways, therefore patients with liver impairment may be at risk of accumulating methadone after multiple dosing.

Gender

The pharmacokinetics of methadone have not been evaluated for gender specificity.

Race

The pharmacokinetics of methadone have not been evaluated for race specificity.

Geriatric

The pharmacokinetics of methadone have not been evaluated in the geriatric population.

Pediatric

The pharmacokinetics of methadone have not been evaluated in the pediatric population.

Drug Interactions

(see PRECAUTIONS : Drug Interactions) Methadone undergoes hepatic N-demethylation by cytochrome P-450 isoforms, principally CYP3A4, CYP2B6, CYP2C19, and to a lesser extent by CYP2C9 and CYP2D6. Coadministration of methadone with inducers of these enzymes may result in more rapid methadone metabolism, and potentially, decreased effects of methadone. Conversely, administration with CYP inhibitors may reduce metabolism and potentiate methadone’s effects. Pharmacokinetics of methadone may be unpredictable when coadministered with drugs that are known to both induce and inhibit CYP enzymes. Although antiretroviral drugs such as efavirenz, nelfinavir, nevirapine, ritonavir, lopinavir+ritonavir combination are known to inhibit some CYPs, they are shown to reduce the plasma levels of methadone, possibly due to their CYP induction activity. Therefore, drugs administered concomitantly with methadone should be evaluated for interaction potential; clinicians are advised to evaluate individual response to drug therapy before making a dosage adjustment.

INDICATIONS AND USAGE

1. For detoxification treatment of opioid addiction (heroin or other morphine-like drugs).
2. For maintenance treatment of opioid addiction (heroin or other morphine-like drugs), in conjunction with appropriate social and medical services.

NOTE

Outpatient maintenance and outpatient detoxification treatment may be provided only by Opioid Treatment Programs (OTPs) certified by the Federal Substance Abuse and Mental Health Services Administration (SAMHSA) and registered by the Drug Enforcement Administration (DEA). This does not preclude the maintenance treatment of a patient with concurrent opioid addiction who is hospitalized for conditions other than opioid addiction and who requires temporary maintenance during the critical period of his/her stay, or of a patient whose enrollment has been verified in a program which has been certified for maintenance treatment with methadone.

CONTRAINDICATIONS

Methadone hydrochloride oral concentrate is contraindicated in patients with a known hypersensitivity to methadone hydrochloride or any other ingredient in methadone hydrochloride oral concentrate.

Methadone hydrochloride oral concentrate is contraindicated in any situation where opioids are contraindicated such as: patients with respiratory depression (in the absence of resuscitative equipment or in unmonitored settings), and in patients with acute bronchial asthma or hypercarbia.

Methadone is contraindicated in any patient who has or is suspected of having a paralytic ileus.

WARNINGS

Methadone hydrochloride oral concentrate is for oral administration only. The preparation must not be injected. Methadone hydrochloride oral concentrate, if dispensed, should be packaged in child-resistant containers and kept out of reach of children to prevent accidental ingestion.

Respiratory Depression

Respiratory depression is the chief hazard associated with methadone hydrochloride administration. Methadone's peak respiratory depressant effects typically occur later, and persist longer than its peak analgesic effects, in the short-term use setting. These characteristics can contribute to cases of iatrogenic overdose, particularly during treatment initiation and dose titration.

Respiratory depression is of particular concern in elderly or debilitated patients as well as in those suffering from conditions accompanied by hypoxia or hypercapnia when even moderate therapeutic doses may dangerously decrease pulmonary ventilation.

Methadone should be administered with extreme caution to patients with conditions accompanied by hypoxia, hypercapnia, or decreased respiratory reserve such as: asthma, chronic obstructive pulmonary disease or cor pulmonale, severe obesity, sleep apnea syndrome, myxedema, kyphoscoliosis, and central nervous system (CNS) depression or coma. In these patients, even usual therapeutic doses of methadone may decrease respiratory drive while simultaneously increasing airway resistance to the point of apnea. Methadone should be used at the lowest effective dose and only under careful medical supervision.

Cardiac Conduction Effects

This information is intended to alert the prescriber to comprehensively evaluate the risks and benefits of methadone treatment. The intent is not to deter the appropriate use of methadone in patients with a history of cardiac disease.

Laboratory studies, both in vivo and in vitro, have demonstrated that methadone inhibits cardiac potassium channels and prolongs the QT interval. Cases of QT interval prolongation and serious arrhythmia (torsades de pointes) have been observed during treatment with methadone. These cases appear to be more commonly associated with, but not limited to, higher dose treatment (> 200 mg/day). Although most cases involve patients being treated for pain with large, multiple daily doses of methadone, cases have been reported in patients receiving doses commonly used for maintenance treatment of opioid addiction. In most of the cases seen at typical maintenance doses, concomitant medications and/or clinical conditions such as hypokalemia were noted as contributing factors. However, the evidence strongly suggests that methadone possesses the potential for adverse cardiac conduction effects in some patients.

Methadone should be administered with particular caution to patients already at risk for development of prolonged QT interval (e.g., cardiac hypertrophy, concomitant diuretic use, hypokalemia, hypomagnesemia). Careful monitoring is recommended when using methadone in patients with a history of cardiac conduction abnormalities, those taking medications affecting cardiac conduction, and in other cases where history or physical exam suggest an increased risk of dysrhythmia. QT prolongation has also been reported in patients with no prior cardiac history who have received high doses of methadone. Patients developing QT prolongation while on methadone treatment should be evaluated for the presence of modifiable risk factors, such as concomitant medications with cardiac effects, drugs which might cause electrolyte abnormalities and drugs which might act as inhibitors of methadone metabolism.

The potential risks of methadone, including the risk of life-threatening arrhythmias, should be weighed against the risks of discontinuing methadone treatment. In the patient being treated for opiate dependence with methadone maintenance therapy, these risks include a very high likelihood of relapse to illicit drug use following methadone discontinuation.

The use of methadone in patients already known to have a prolonged QT interval has not been systematically studied. The potential risks of methadone should be weighed against the substantial morbidity and mortality associated with untreated opioid addiction.

When treating patients with methadone, an individualized benefit to risk assessment should be carried out and should include evaluation of patient presentation and complete medical history. For patients judged to be at risk, careful monitoring of cardiovascular status, including evaluation of QT prolongation and dysrhythmias should be performed.

Incomplete Cross-Tolerance Between Methadone and Other Opioids

Patients tolerant to other opioids may be incompletely tolerant to methadone. Incomplete cross-tolerance is of particular concern for patients tolerant to other mu-opioid agonists who are being converted to methadone, thus making determination of dosing during opioid conversion complex. Deaths have been reported during conversion from chronic, high-dose treatment with other opioid agonists. A high degree of "opioid tolerance" does not eliminate the possibility of methadone overdose, iatrogenic or otherwise.

Misuse, Abuse, and Diversion of Opioids

Methadone is a mu-agonist opioid with an abuse liability similar to that of morphine and other opioid agonists and is a Schedule II controlled substance. Methadone, like morphine and other opioids used for analgesia, has the potential for being abused and is subject to criminal diversion.

Methadone can be abused in a manner similar to other opioid agonists, legal or illicit. This should be considered when prescribing or dispensing methadone hydrochloride oral concentrate in situations where the clinician is concerned about an increased risk of misuse, abuse, or diversion. Abuse of methadone poses a risk of overdose and death. This risk is increased with concurrent abuse of methadone with alcohol and other substances. In addition, parenteral drug abuse is commonly associated with transmission of infectious diseases such as hepatitis and HIV.

Healthcare professionals should contact their State Professional Licensing Board or State Controlled Substances Authority for information on how to prevent and detect abuse or diversion of this product.

Interactions with Other CNS Depressants

Patients receiving other opioid analgesics, general anesthetics, phenothiazines or other tranquilizers, sedatives, hypnotics, or other CNS depressants (including alcohol) concomitantly with methadone may experience respiratory depression, hypotension, profound sedation, or coma (see PRECAUTIONS).

Interactions with Alcohol and Drugs of Abuse

Methadone may be expected to have additive effects when used in conjunction with alcohol, other opioids, or illicit drugs that cause central nervous system depression. Deaths associated with illicit use of methadone frequently have involved concomitant benzodiazepine abuse.

Head Injury and Increased Intracranial Pressure

The respiratory depressant effects of opioids and their capacity to elevate cerebrospinal-fluid pressure may be markedly exaggerated in the presence of head injury, other intracranial lesions or a pre-existing increase in intracranial pressure. Furthermore, opioids produce effects which may obscure the clinical course of patients with head injuries. In such patients, methadone must be used with caution, and only if it is deemed essential.

Acute Abdominal Conditions

The administration of opioids may obscure the diagnosis or clinical course of patients with acute abdominal conditions.

Hypotensive Effect

The administration of methadone may result in severe hypotension in patients whose ability to maintain normal blood pressure is compromised (e.g., severe volume depletion).

PRECAUTIONS

Methadone should be used with caution in elderly and debilitated patients; patients who are known to be sensitive to central nervous system depressants, such as those with cardiovascular, pulmonary, renal, or hepatic disease; and in patients with comorbid conditions or concomitant medications which may predispose to dysrhythmia or reduced ventilatory drive.

Drug Interactions

In vitro results suggest that methadone undergoes hepatic N-demethylation by cytochrome P450 enzymes, principally CYP3A4, CYP2B6, CYP2C19, and to a lesser extent by CYP2C9 and CYP2D6. Coadministration of methadone with inducers of these enzymes may result in a more rapid metabolism and potential for decreased effects of methadone, whereas administration with CYP inhibitors may reduce metabolism and potentiate methadone’s effects. Although antiretroviral drugs such as efavirenz, nelfinavir, nevirapine, ritonavir, lopinavir+ritonavir combination are known to inhibit CYPs, they are shown to reduce the plasma levels of methadone, possibly due to their CYP induction activity. Therefore, drugs administered concomitantly with methadone should be evaluated for interaction potential; clinicians are advised to evaluate individual response to drug therapy.

Opioid Antagonists, Mixed Agonist/Antagonists, and Partial Agonists

As with other mu-agonists, patients maintained on methadone may experience withdrawal symptoms when given opioid antagonists, mixed agonist/antagonists, and partial agonists. Examples of such agents are naloxone, naltrexone, pentazocine, nalbuphine, butorphanol, and buprenorphine.

Antiretroviral Agents

Abacavir, amprenavir, efavirenz, nelfinavir, nevirapine, ritonavir, lopinavir+ritonavir combination

Coadministration of these antiretroviral agents resulted in increased clearance or decreased plasma levels of methadone. Methadone-maintained patients beginning treatment with these antiretroviral drugs should be monitored for evidence of withdrawal effects and methadone dose should be adjusted accordingly.

Didanosine and Stavudine

Experimental evidence demonstrated that methadone decreased the area under the concentration-time curve (AUC) and peak levels for didanosine and stavudine, with a more significant decrease for didanosine. Methadone disposition was not substantially altered.

Zidovudine

Experimental evidence demonstrated that methadone increased the AUC of zidovudine which could result in toxic effects.

Cytochrome P450 Inducers

Methadone-maintained patients beginning treatment with CYP3A4 inducers should be monitored for evidence of withdrawal effects and methadone dose should be adjusted accordingly. The following drug interactions were reported following coadministration of methadone with inducers of cytochrome P450 enzymes:

Rifampin

In patients well-stabilized on methadone, concomitant administration of rifampin resulted in a marked reduction in serum methadone levels and a concurrent appearance of withdrawal symptoms.

Phenytoin

In a pharmacokinetic study with patients on methadone maintenance therapy, phenytoin administration (250 mg b.i.d. initially for 1 day followed by 300 mg QD for 3 to 4 days) resulted in an approximately 50% reduction in methadone exposure and withdrawal symptoms occurred concurrently. Upon discontinuation of phenytoin, the incidence of withdrawal symptoms decreased and methadone exposure increased to a level comparable to that prior to phenytoin administration.

St. John’s Wort, Phenobarbital, Carbamazepine

Administration of methadone along with other CYP3A4 inducers may result in withdrawal symptoms.

Cytochrome P450 Inhibitors

Since the metabolism of methadone is mediated primarily by CYP3A4 isozyme, coadministration of drugs that inhibit CYP3A4 activity may cause decreased clearance of methadone. The expected clinical results would be increased or prolonged opioid effects. Thus, methadone-treated patients coadministered strong inhibitors of CYP3A4, such as azole antifungal agents (e.g., ketoconazole) and macrolide antibiotics (e.g., erythromycin), with methadone should be carefully monitored and dosage adjustment should be undertaken if warranted. Some selective serotonin reuptake inhibitors (SSRIs) (e.g., sertraline, fluvoxamine) may increase methadone plasma levels upon coadministration with methadone and result in increased opiate effects and/or toxicity.

Voriconazole

Repeat dose administration of oral voriconazole (400 mg Q12h for 1 day, then 200 mg Q12h for 4 days) increased the Cmax and AUC of (R)-methadone by 31% and 47%, respectively, in subjects receiving a methadone maintenance dose (30 to 100 mg QD). The Cmax and AUC of (S)-methadone increased by 65% and 103%, respectively. Increased plasma concentrations of methadone have been associated with toxicity including QT prolongation. Frequent monitoring for adverse events and toxicity related to methadone is recommended during coadministration. Dose reduction of methadone may be needed.

Others

Monoamine Oxidase (MAO) Inhibitors

Therapeutic doses of meperidine have precipitated severe reactions in patients concurrently receiving monoamine oxidase inhibitors or those who have received such agents within 14 days. Similar reactions thus far have not been reported with methadone. However, if the use of methadone is necessary in such patients, a sensitivity test should be performed in which repeated small, incremental doses of methadone are administered over the course of several hours while the patient's condition and vital signs are under careful observation.

Desipramine

PBlood levels of desipramine have increased with concurrent methadone administration.

Potentially Arrhythmogenic Agents

Extreme caution is necessary when any drug known to have the potential to prolong the QT interval is prescribed in conjunction with methadone. Pharmacodynamic interactions may occur with concomitant use of methadone and potentially arrhythmogenic agents such as class I and III antiarrhythmics, some neuroleptics and tricyclic antidepressants, and calcium channel blockers.

Caution should also be exercised when treating methadone patients concomitantly with drugs capable of inducing electrolyte disturbances (hypomagnesemia, hypokalemia) that may prolong the QT interval. These drugs include diuretics, laxatives, and, in rare cases, mineralocorticoid hormones.

Interactions with Alcohol and Drugs of Abuse

Methadone may be expected to have additive effects when used in conjunction with alcohol, other opioids or CNS depressants, or with illicit drugs that cause central nervous system depression. Deaths have been reported when methadone has been abused in conjunction with benzodiazepines.

Anxiety

Since methadone as used by tolerant patients at a constant maintenance dosage does not act as a tranquilizer, patients will react to life problems and stresses with the same symptoms of anxiety as do other individuals. The physician should not confuse such symptoms with those of narcotic abstinence and should not attempt to treat anxiety by increasing the dose of methadone. The action of methadone in maintenance treatment is limited to the control of narcotic withdrawal symptoms and is ineffective for relief of general anxiety.

Acute Pain

Patients in methadone maintenance treatment for opioid dependence who experience physical trauma, postoperative pain or other acute pain cannot be expected to derive analgesia from their existing dose of methadone. Such patients should be administered analgesics, including opioids, in doses that would otherwise be indicated for non-methadone-treated patients with similar painful conditions. Due to the opioid tolerance induced by methadone, when opioids are required for management of acute pain in methadone patients, somewhat higher and/or more frequent doses will often be required than would be the case for non-tolerant patients.

Physical Dependence

Physical dependence is manifested by withdrawal symptoms after abrupt discontinuation of a drug or upon administration of an antagonist. Physical dependence is expected during opioid agonist therapy of opioid addiction.

If a physically dependent patient abruptly discontinues use of methadone, or the dose of methadone does not adequately “cover” the patient, an opioid abstinence or withdrawal syndrome may develop and is characterized by some or all of the following: restlessness, lacrimation, rhinorrhea, yawning, perspiration, chills, myalgia, and mydriasis. Other symptoms may also develop, including irritability, anxiety, backache, joint pain, weakness, abdominal cramps, insomnia, nausea, anorexia, vomiting, diarrhea, or increased blood pressure, respiratory rate, or heart rate.

Infants born to mothers physically dependent on opioids may also be physically dependent and may exhibit respiratory difficulties and withdrawal symptoms (see PRECAUTIONS : Pregnancy, Labor and Delivery).

In general, opioids should not be abruptly discontinued (see DOSAGE AND ADMINISTRATION: For Medically Supervised Withdrawal After a Period of Maintenance Treatment).

Special-Risk Patients

Methadone should be given with caution, and the initial dose reduced, in certain patients such as the elderly and debilitated, and those with severe impairment of hepatic or renal function, hypothyroidism, Addison’s disease, prostatic hypertrophy, or urethral stricture. The usual precautions should be observed and the possibility of respiratory depression requires added vigilance.

Information for Patients

- Patients should be cautioned that methadone, like all opioids, may impair the mental and/or physical abilities required for the performance of potentially hazardous tasks such as driving or operating machinery.
- Patients who are ambulatory should be cautioned that methadone, like other opioids, may produce orthostatic hypotension.
- Patients should be cautioned that alcohol and other CNS depressants may produce an additive CNS depression when taken with this product and should be avoided.
- Patients should be instructed to seek medical attention immediately if they experience symptoms suggestive of an arrhythmia (such as palpitations, dizziness, lightheadedness, or syncope) when taking methadone.
- Patients initiating treatment with methadone should be reassured that the dose of methadone will “hold” for longer periods of time as treatment progresses.
- Patients should be instructed to keep methadone in a secure place out of the reach of children and other household members. Accidental or deliberate ingestion by a child may cause respiratory depression that can result in death.
- Patients should be advised not to change the dose of methadone without consulting their physician.
- Women of childbearing potential who become or are planning to become pregnant should be advised to consult their physicians regarding the effects of methadone use during pregnancy.
- If a physically dependent patient abruptly discontinues use of methadone, an opioid abstinence or withdrawal syndrome may develop. If cessation of therapy is indicated, it may be appropriate to taper the methadone dose, rather than abruptly discontinue it, due to the risk of precipitating withdrawal symptoms. Their physician can provide a dose schedule to accomplish a gradual discontinuation of the medication.
- Patients seeking to discontinue treatment with methadone for opioid dependence should be apprised of the high risk of relapse to illicit drug use associated with discontinuation of methadone maintenance treatment.
- Patients should be advised that methadone is a potential drug of abuse. They should protect it from theft, and it should never be given to anyone other than the individual for whom it was prescribed.
- Breastfeeding:
- 1. Methadone use is usually compatible with breastfeeding. Pregnant mothers using methadone should be counseled about the benefits and risks of breastfeeding while using methadone. Counseling should include the following information:
- • The baby receives a small amount of methadone through breastmilk.
- • The baby may experience methadone withdrawal if breastfeeding is discontinued suddenly. Patients discontinuing breastfeeding should develop a plan to wean with the baby's healthcare team.
- • Use of other substances of abuse during breastfeeding will expose the baby to additional risks. Patients who use other substances of abuse should not breastfeed.
- 2. When starting methadone for the first time or increasing the dose, breastfeeding patients should watch their babies closely for changes in behavior or breathing patterns.

Carcinogenesis, Mutagenesis, Impairment of Fertility

Carcinogenesis

The results of carcinogenicity assessment in B6C2F1 mice and Fischer 344 rats following dietary administration of two doses of methadone HCl have been published. Mice consumed 15 mg/kg/day or 60 mg/kg/day methadone for two years. These doses were approximately 0.6 and 2.5 times a human daily oral dose of 120 mg/day on a body surface area basis (mg/m^2). There was a significant increase in pituitary adenomas in female mice treated with 15 mg/kg/day but not with 60 mg/kg/day. Under the conditions of the assay, there was no clear evidence for a treatment-related increase in the incidence of neoplasms in male rats. Due to decreased food consumption in males at the high dose, male rats consumed 16 mg/kg/day and 28 mg/kg/day of methadone for two years. These doses were approximately 1.3 and 2.3 times a human daily oral dose of 120 mg/day, based on body surface area comparison. In contrast, female rats consumed 46 mg/kg/day or 88 mg/kg/day for two years. These doses were approximately 3.7 and 7.1 times a human daily oral dose of 120 mg/day, based on body surface area comparison. Under the conditions of the assay, there was no clear evidence for a treatment-related increase in the incidence of neoplasms in either male or female rats.

Mutagenesis

There are several published reports on the potential genetic toxicity of methadone. Methadone tested negative in tests for chromosome breakage and disjunction and sex-linked recessive lethal gene mutations in germ cells of Drosophila using feeding and injection procedures. In contrast, methadone tested positive in the in vivo mouse dominant lethal assay and the in vivo mammalian spermatogonial chromosome aberration test. Additionally, methadone tested positive in the E.coli DNA repair system and Neurospora crassa and mouse lymphoma forward mutation assays.

Fertility

Reproductive function in human males may be decreased by methadone treatment. Reductions in ejaculate volume and seminal vesicle and prostate secretions have been reported in methadone-treated individuals. In addition, reductions in serum testosterone levels and sperm motility, and abnormalities in sperm morphology have been reported. Published animal studies provide additional data indicating that methadone treatment of males can alter reproductive function. Methadone produces a significant regression of sex accessory organs and testes of male mice and rats. Additional data have been published indicating that methadone treatment of male rats (once a day for three consecutive days) increased embryolethality and neonatal mortality. Examination of uterine contents of methadone-naive female mice bred to methadone-treated mice indicated that methadone treatment produced an increase in the rate of preimplantation deaths in all post-meiotic states.

Pregnancy

Teratogenic Effects

Pregnancy Category C

There are no controlled studies of methadone use in pregnant women that can be used to establish safety. However, an expert review of published data on experiences with methadone use during pregnancy by the Teratogen Information System (TERIS) concluded that maternal use of methadone during pregnancy as part of a supervised, therapeutic regimen is unlikely to pose a substantial teratogenic risk (quantity and quality of data assessed as “limited to fair”). However, the data are insufficient to state that there is no risk (TERIS, last reviewed October, 2002). Pregnant women involved in methadone maintenance programs have been reported to have significantly improved prenatal care leading to significantly reduced incidence of obstetric and fetal complications and neonatal morbidity and mortality when compared to women using illicit drugs. Several factors complicate the interpretation of investigations of the children of women who take methadone during pregnancy. These include the maternal use of illicit drugs, other maternal factors such as nutrition, infection, and psychosocial circumstances, limited information regarding dose and duration of methadone use during pregnancy, and the fact that most maternal exposure appears to occur after the first trimester of pregnancy. Reported studies have generally compared the benefit of methadone to the risk of untreated addiction to illicit drugs.

Methadone has been detected in amniotic fluid and cord plasma at concentrations proportional to maternal plasma and in newborn urine at lower concentrations than corresponding maternal urine.

A retrospective series of 101 pregnant, opiate-dependent women who underwent inpatient opiate detoxification with methadone did not demonstrate any increased risk of miscarriage in the second trimester or premature delivery in the third trimester.

Several studies have suggested that infants born to narcotic-addicted women treated with methadone during all or part of pregnancy have been found to have decreased fetal growth with reduced birth weight, length, and/or head circumference compared to controls. This growth deficit does not appear to persist into later childhood. However, children born to women treated with methadone during pregnancy have been shown to demonstrate mild but persistent deficits in performance on psychometric and behavioral tests.

Additional information on the potential risks of methadone may be derived from animal data. Methadone does not appear to be teratogenic in the rat or rabbit models. However, following large doses, methadone produced teratogenic effects in the guinea pig, hamster and mouse. One published study in pregnant hamsters indicated that a single subcutaneous dose of methadone ranging from 31 to 185 mg/kg (the 31 mg/kg dose is approximately 2 times a human daily oral dose of 120 mg/day on a mg/m^2 basis) on day 8 of gestation resulted in a decrease in the number of fetuses per litter and an increase in the percentage of fetuses exhibiting congenital malformations described as exencephaly, cranioschisis, and “various other lesions.” The majority of the doses tested also resulted in maternal death. In another study, a single subcutaneous dose of 22 to 24 mg/kg methadone (estimated exposure was approximately equivalent to a human daily oral dose of 120 mg/day on a mg/m^2 basis) administered on day 9 of gestation in mice also produced exencephaly in 11% of the embryos. However, no effects were reported in rats and rabbits at oral doses up to 40 mg/kg (estimated exposure was approximately 3 and 6 times, respectively, a human daily oral dose of 120 mg/day on a mg/m^2 basis) administered during days 6 to 15 and 6 to 18, respectively.

Nonteratogenetic Effects

Babies born to mothers who have been taking opioids regularly prior to delivery may be physically dependent. Onset of withdrawal symptoms in infants is usually in the first days after birth. Withdrawal signs in the newborn include irritability and excessive crying, tremors, hyperactive reflexes, increased respiratory rate, increased stools, sneezing, yawning, vomiting, and fever. The intensity of the syndrome does not always correlate with the maternal dose or the duration of maternal exposure. The duration of the withdrawal signs may vary from a few days to weeks or even months. There is no consensus on the appropriate management of infant withdrawal.

There are conflicting reports on whether SIDS occurs with an increased incidence in infants born to women treated with methadone during pregnancy.

Abnormal fetal nonstress tests (NSTs) have been reported to occur more frequently when the test is performed 1 to 2 hours after a maintenance dose of methadone in late pregnancy compared to controls.

Published animal data have reported increased neonatal mortality in the offspring of male rats that were treated with methadone prior to mating. In these studies, the female rats were not treated with methadone, indicating paternally-mediated developmental toxicity. Specifically, methadone administered to the male rat prior to mating with methadone-naïve females resulted in decreased weight gain in progeny after weaning. The male progeny demonstrated reduced thymus weights, whereas the female progeny demonstrated increased adrenal weights. Furthermore, behavioral testing of these male and female progeny revealed significant differences in behavioral tests compared to control animals, suggesting that paternal methadone exposure can produce physiological and behavioral changes in progeny in this model. Other animal studies have reported that perinatal exposure to opioids including methadone alters neuronal development and behavior in the offspring. Perinatal methadone exposure in rats has been linked to alterations in learning ability, motor activity, thermal regulation, nociceptive responses and sensitivity to drugs. Additional animal data demonstrates evidence for neurochemical changes in the brains of methadone-treated offspring, including changes to the cholinergic, dopaminergic, noradrenergic and serotonergic systems. Additional studies demonstrated that methadone treatment of male rats for 21 to 32 days prior to mating with methadone-naïve females did not produce any adverse effects, suggesting that prolonged methadone treatment of the male rat resulted in tolerance to the developmental toxicities noted in the progeny. Mechanistic studies in this rat model suggest that the developmental effects of “paternal” methadone on the progeny appear to be due to decreased testosterone production. These animal data mirror the reported clinical findings of decreased testosterone levels in human males on methadone maintenance therapy for opioid addiction and in males receiving chronic intraspinal opioids.

Clinical Pharmacology in Pregnancy

Pregnant women appear to have significantly lower trough plasma methadone concentrations, increased plasma methadone clearance, and shorter methadone half-life than after delivery. Dosage adjustment using higher doses or administering the daily dose in divided doses may be necessary in pregnant women treated with methadone. (See CLINICAL PHARMACOLOGY and DOSAGE AND ADMINISTRATION).

Methadone should be used during pregnancy only if the potential benefit justifies the potential risk to the fetus.

Labor and Delivery

As with all opioids, administration of this product to the mother shortly before delivery may result in some degree of respiratory depression in the newborn, especially if higher doses are used. Methadone is not recommended for obstetric analgesia because its long duration of action increases the probability of respiratory depression in the newborn. Narcotics with mixed agonist-antagonist properties should not be used for pain control during labor in patients chronically treated with methadone as they may precipitate acute withdrawal.

Nursing Mothers

Methadone is secreted into human milk. At maternal oral doses of 10 to 80 mg/day, methadone concentrations from 50 to 570 mcg/L in milk have been reported, which, in the majority of samples, were lower than maternal serum drug concentrations at steady state. Peak methadone levels in milk occur approximately 4 to 5 hours after an oral dose. Based on an average milk consumption of 150 mL/kg/day, an infant would consume approximately 17.4 mcg/kg/day which is approximately 2 to 3% of the oral maternal dose. Methadone has been detected in very low plasma concentrations in some infants whose mothers were taking methadone.

Caution should be exercised when methadone is administered to a nursing woman. There have been rare cases of sedation and respiratory depression in infants exposed to methadone through breast milk.

Mothers using methadone should receive specific information about how to identify respiratory depression and sedation in their babies. They should know when to contact their healthcare provider or seek immediate medical care. A healthcare provider should weigh the benefits of breastfeeding against the risks of infant exposure to methadone and possible exposure to other medicines.

Women being treated with methadone for any indication who are already breastfeeding should be counseled to wean breastfeeding gradually in order to prevent the development of withdrawal symptoms in the infant.

Methadone Maintenance Treatment for Opioid Dependence During Breastfeeding

Women on methadone maintenance therapy, who express a desire to breastfeed, should be informed of the risks and benefits of breastfeeding during pregnancy and immediately postpartum. The patient should clearly understand that, while breastfeeding, she should not use illicit substances or any other drug not prescribed by her healthcare provider. She should understand the reasons why use of additional drugs can increase risk to her breastfeeding infant beyond any risk from methadone.

Pediatric Use

Safety and effectiveness in pediatric patients below the age of 18 years have not been established.

Accidental or deliberate ingestion by a child may cause respiratory depression that can result in death. Patients and caregivers should be instructed to keep methadone in a secure place out of the reach of children and to discard unused methadone in such a way that individuals other than the patient for whom it was originally prescribed will not come in contact with the drug.

Geriatric Use

Clinical studies of methadone did not include sufficient numbers of subjects aged 65 and over to determine whether they respond differently compared to younger subjects. Other reported clinical experience has not identified differences in responses between elderly and younger patients. In general, dose selection for elderly patients should be cautious, usually starting at the low end of the dosing range, reflecting the greater frequency of decreased hepatic, renal, or cardiac function and of concomitant disease or other drug therapy.

Renal Impairment

The use of methadone has not been extensively evaluated in patients with renal insufficiency.

Hepatic Impairment

The use of methadone has not been extensively evaluated in patients with hepatic insufficiency. Methadone is metabolized in the liver and patients with liver impairment may be at risk of accumulating methadone after multiple dosing.

Gender

The use of methadone has not been evaluated for gender specificity.

ADVERSE REACTIONS

Heroin Withdrawal

During the induction phase of methadone maintenance treatment, patients are being withdrawn from heroin and may therefore show typical withdrawal symptoms, which should be differentiated from methadone-induced side effects. They may exhibit some or all of the following signs and symptoms associated with acute withdrawal from heroin or other opiates: lacrimation, rhinorrhea, sneezing, yawning, excessive perspiration, goose-flesh, fever, chilliness alternating with flushing, restlessness, irritability, weakness, anxiety, depression, dilated pupils, tremors, tachycardia, abdominal cramps, body aches, involuntary twitching and kicking movements, anorexia, nausea, vomiting, diarrhea, intestinal spasms, and weight loss.

Initial Administration

The initial methadone dose should be carefully titrated to the individual. Too rapid titration for the patient’s sensitivity is more likely to produce adverse effects.

The major hazards of methadone are respiratory depression and, to a lesser degree, systemic hypotension. Respiratory arrest, shock, cardiac arrest, and death have occurred.

The most frequently observed adverse reactions include lightheadedness, dizziness, sedation, nausea, vomiting, and sweating. These effects seem to be more prominent in ambulatory patients and in those who are not suffering severe pain. In such individuals, lower doses are advisable.

Other adverse reactions include the following: (listed alphabetically under each subsection)

Body as a Whole: asthenia (weakness), edema, headache

Cardiovascular:(also see WARNINGS: Cardiac Conduction Effects): arrhythmias, bigeminal rhythms, bradycardia, cardiomyopathy, ECG abnormalities, extrasystoles, flushing, heart failure, hypotension, palpitations, phlebitis, QT interval prolongation, syncope, T-wave inversion, tachycardia, torsade de pointes, ventricular fibrillation, ventricular tachycardia

Digestive: abdominal pain, anorexia, biliary tract spasm, constipation, dry mouth, glossitis

Hematologic and Lymphatic: reversible thrombocytopenia has been described in opioid addicts with chronic hepatitis

Metabolic and Nutritional: hypokalemia, hypomagnesemia, weight gain

Nervous: agitation, confusion, disorientation, dysphoria, euphoria, insomnia, seizures

Respiratory: pulmonary edema, respiratory depression (see WARNINGS: Respiratory Depression)

Skin and Appendages: pruritis, urticaria, other skin rashes, and rarely, hemorrhagic urticaria

Special Senses: hallucinations, visual disturbances

Urogenital: amenorrhea, antidiuretic effect, reduced libido and/or potency, urinary retention or hesitancy

Maintenance on a Stabilized Dose

During prolonged administration of methadone, as in a methadone maintenance treatment program, there is usually a gradual, yet progressive, disappearance of side effects over a period of several weeks. However, constipation and sweating often persist.

DRUG ABUSE AND DEPENDENCE

Methadone hydrochloride oral concentrate contains methadone, a potent Schedule II opioid agonist. Schedule II opioid substances, which also include hydromorphone, morphine, oxycodone, and oxymorphone, have the highest potential for abuse and risk of fatal overdose due to respiratory depression. Methadone, like morphine and other opioids used for analgesia, has the potential for being abused and is subject to criminal diversion.

Abuse of methadone poses a risk of overdose and death. This risk is increased with concurrent abuse of methadone with alcohol and other substances. In addition, parenteral drug abuse is commonly associated with transmission of infectious disease such as hepatitis and HIV.

Since methadone may be diverted for non-medical use, careful record keeping of ordering and dispensing information, including quantity, frequency, and renewal requests is strongly advised.

Proper assessment of the patient, proper prescribing practices, periodic re-evaluation of therapy, and proper dispensing and storage are appropriate measures that help to limit abuse of opioid drugs.

Methadone, when used for the treatment of opioid addiction in detoxification or maintenance programs, may be dispensed only by opioid treatment programs certified by the Substance Abuse and Mental Health Services Administration (and agencies, practitioners or institutions by formal agreement with the program sponsor).

Infants born to mothers physically dependent on opioids may also be physically dependent and may exhibit respiratory difficulties and withdrawal symptoms (See PRECAUTIONS : Pregnancy, Labor and Delivery).

OVERDOSAGE

Signs and Symptoms

Serious overdosage of methadone is characterized by respiratory depression (a decrease in respiratory rate and/or tidal volume, Cheyne-Stokes respiration, cyanosis), extreme somnolence progressing to stupor or coma, maximally constricted pupils, skeletal-muscle flaccidity, cold and clammy skin, and sometimes, bradycardia and hypotension. In severe overdosage, particularly by the intravenous route, apnea, circulatory collapse, cardiac arrest, and death may occur.

Treatment

Primary attention should be given to the reestablishment of adequate respiratory exchange through provision of a patent airway and institution of assisted or controlled ventilation. If a non-tolerant person takes a large dose of methadone, effective opioid antagonists are available to counteract the potentially lethal respiratory depression. The physician must remember, however, that methadone is a long-acting depressant (36 to 48 hours), whereas opioid antagonists act for much shorter periods (one to three hours). The patient must, therefore, be monitored continuously for recurrence of respiratory depression and may need to be treated repeatedly with the narcotic antagonist.

Opioid antagonists should not be administered in the absence of clinically significant respiratory or cardiovascular depression. In an individual physically dependent on opioids, the administration of the usual dose of an opioid antagonist may precipitate an acute withdrawal syndrome. The severity of this syndrome will depend on the degree of physical dependence and the dose of the antagonist administered. If antagonists must be used to treat serious respiratory depression in the physically dependent patient, the antagonist should be administered with extreme care and by titration with smaller than usual doses of the antagonist.

Intravenously administered naloxone or nalmefene may be used to reverse signs of intoxication. Because of the relatively short half-life of naloxone as compared with methadone, repeated injections may be required until the status of the patient remains satisfactory. Naloxone may also be administered by continuous intravenous infusion.

Oxygen, intravenous fluids, vasopressors, and other supportive measures should be employed as indicated.

DOSAGE AND ADMINISTRATION

Methadone differs from many other opioid agonists in several important ways. Methadone's pharmacokinetic properties, coupled with high interpatient variability in its absorption, metabolism, and relative analgesic potency, necessitate a cautious and highly individualized approach to prescribing. Particular vigilance is necessary during treatment initiation, during conversion from one opioid to another, and during dose titration.

While methadone’s duration of analgesic action (typically 4 to 8 hours) in the setting of single-dose studies approximates that of morphine, methadone’s plasma elimination half-life is substantially longer than that of morphine (typically 8 to 59 hours vs. 1 to 5 hours). Methadone's peak respiratory depressant effects typically occur later, and persist longer than its peak analgesic effects. Also, with repeated dosing, methadone may be retained in the liver and then slowly released, prolonging the duration of action despite low plasma concentrations. For these reasons, steady-state plasma concentrations, and full analgesic effects, are usually not attained until 3 to 5 days of dosing. Additionally, incomplete cross-tolerance between mu-opioid agonists makes determination of dosing during opioid conversion complex.

The complexities associated with methadone dosing can contribute to cases of iatrogenic overdose, particularly during treatment initiation and dose titration. A high degree of "opioid tolerance" does not eliminate the possibility of methadone overdose, iatrogenic or otherwise. Deaths have been reported during conversion to methadone from chronic, high-dose treatment with other opioid agonists and during initiation of methadone treatment of addiction in subjects previously abusing high doses of other agonists.

Detoxification and Maintenance Treatment of Opiate Dependence

For detoxification and maintenance of opiate dependence methadone should be administered in accordance with the treatment standards cited in 42 CFR Section 8.12, including limitations on unsupervised administration.

Induction/Initial Dosing

The initial methadone dose should be administered, under supervision, when there are no signs of sedation or intoxication, and the patient shows symptoms of withdrawal. Initially, a single dose of 20 to 30 mg of methadone will often be sufficient to suppress withdrawal symptoms. The initial dose should not exceed 30 mg. If same-day dosing adjustments are to be made, the patient should be asked to wait 2 to 4 hours for further evaluation, when peak levels have been reached. An additional 5 to 10 mg of methadone may be provided if withdrawal symptoms have not been suppressed or if symptoms reappear. The total daily dose of methadone on the first day of treatment should not ordinarily exceed 40 mg. Dose adjustments should be made over the first week of treatment based on control of withdrawal symptoms at the time of expected peak activity (e.g., 2 to 4 hours after dosing). Dose adjustment should be cautious; deaths have occurred in early treatment due to the cumulative effects of the first several days’ dosing. Patients should be reminded that the dose will “hold” for a longer period of time as tissue stores of methadone accumulate.

Initial doses should be lower for patients whose tolerance is expected to be low at treatment entry. Loss of tolerance should be considered in any patient who has not taken opioids for more than 5 days. Initial doses should not be determined by previous treatment episodes or dollars spent per day on illicit drug use.

For Short-Term Detoxification

For patients preferring a brief course of stabilization followed by a period of medically supervised withdrawal, it is generally recommended that the patient be titrated to a total daily dose of about 40 mg in divided doses to achieve an adequate stabilizing level. Stabilization can be continued for 2 to 3 days, after which the dose of methadone should be gradually decreased. The rate at which methadone is decreased should be determined separately for each patient. The dose of methadone can be decreased on a daily basis or at 2-day intervals, but the amount of intake should remain sufficient to keep withdrawal symptoms at a tolerable level. In hospitalized patients, a daily reduction of 20% of the total daily dose may be tolerated. In ambulatory patients, a somewhat slower schedule may be needed.

For Maintenance Treatment

Patients in maintenance treatment should be titrated to a dose at which opioid symptoms are prevented for 24 hours, drug hunger or craving is reduced, the euphoric effects of self-administered opioids are blocked or attenuated, and the patient is tolerant to the sedative effects of methadone. Most commonly, clinical stability is achieved at doses between 80 to 120 mg/day.

For Medically Supervised Withdrawal After a Period of Maintenance Treatment

There is considerable variability in the appropriate rate of methadone taper in patients choosing medically supervised withdrawal from methadone treatment. It is generally suggested that dose reductions should be less than 10% of the established tolerance or maintenance dose, and that 10 to 14-day intervals should elapse between dose reductions. Patients should be apprised of the high risk of relapse to illicit drug use associated with discontinuation of methadone maintenance treatment.

HOW SUPPLIED

Methadone Hydrochloride Oral Concentrate USP, (Dye-Free, Sugar-Free, Unflavored)

10 mg per mL is supplied as a clear, colorless, unflavored solution.

NDC 70166-284-01: Box of 30 pre-filled syringes each containing 1mL

NDC 70166-284-02: Box of 30 pre-filled syringes each containing 5mL

Store at 20° to 25°C (68° to 77°F). [See USP Controlled Room Temperature.]

Protect from light.

Rpkg. by:

Lohxa

Worcester, MA 01608

Revised 02/2018